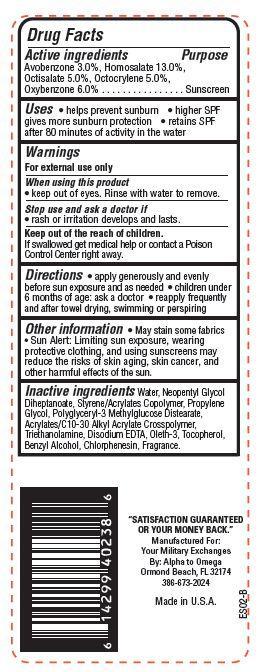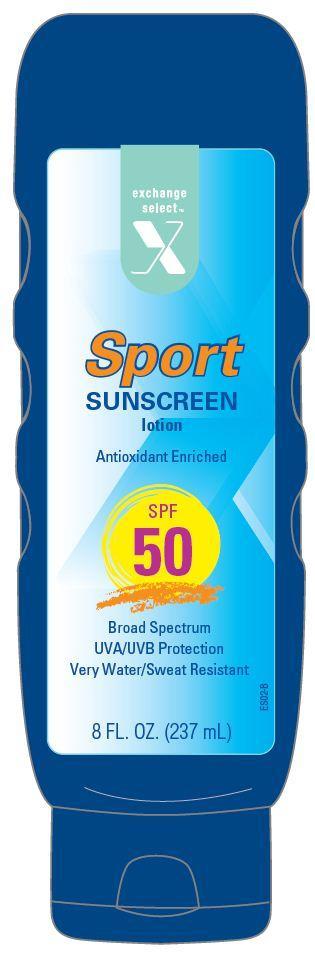 DRUG LABEL: Exchange Select Sport Sunscreen
NDC: 55301-010 | Form: LOTION
Manufacturer: ARMY AND AIR FORCE EXCHANGE SERVICE
Category: otc | Type: HUMAN OTC DRUG LABEL
Date: 20121116

ACTIVE INGREDIENTS: AVOBENZONE 3 g/100 g; HOMOSALATE 13 g/100 g; OCTISALATE 5 g/100 g; OCTOCRYLENE 5 g/100 g; OXYBENZONE 6 g/100 g
INACTIVE INGREDIENTS: WATER; CHLORPHENESIN; PROPYLENE GLYCOL; TROLAMINE; OLETH-3; BENZYL ALCOHOL; TOCOPHEROL; EDETATE DISODIUM

Drug Facts

Active ingredients

Avobenzone 3.0 %

Homosalate 13.0%

Octisalate 5.0%

Octocrylene 5.0%

Oxybenzone 6.0%

Purpose

Sunscreen

Uses

- helps prevent sunburn
- higher SPF gives more sunburn protection
- retains SPF after 80 minutes of activity in the water

Warnings

For external use only

When using this product

- keep out of eyes. Rinse with water to remove.

stop use and ask a doctor if

- rash or irritation develops and lasts.

keep out of reach of children.

If swallowed, get medical help or contact a Poison Control Center right away.

Directions

- apply generously and evenly before sun exposure and as needed
- children under 6 months of age:ask a doctor
- reapply frequently and after towel drying, swimming or perspiring.

Other Information

- May stain some fabrics
- Sun Alert: Limiting sun exposure, wearing, protective clothing, and using sunscreens may reduce the risks of skin aging, skin cancer, and other harmful effects of the sun.

Inactive ingredients

Water, Neopentyl Glycol Diheptanoate, Styrene/Acrylates Copolymer, Propylene Glycol, Polyglyceryl-3 Methylglucose Distearate, Benzyl Alcohol, Acrylates/C10-30 Alkyl Acrylate Crosspolymer, Triethanolamine, Disodium EDTA, Oleth-3, Tocopherol, Chlorphenesin, Fragrance.

Principal Display Panel

EXCHANGE
Select
X
Sport
SUNSCREEN
lotion
SPF 50
Broad Spectrum
UVA/UVB Protection
Very Water/ Sweat Resistant
8 FL.OZ. (237 mL)